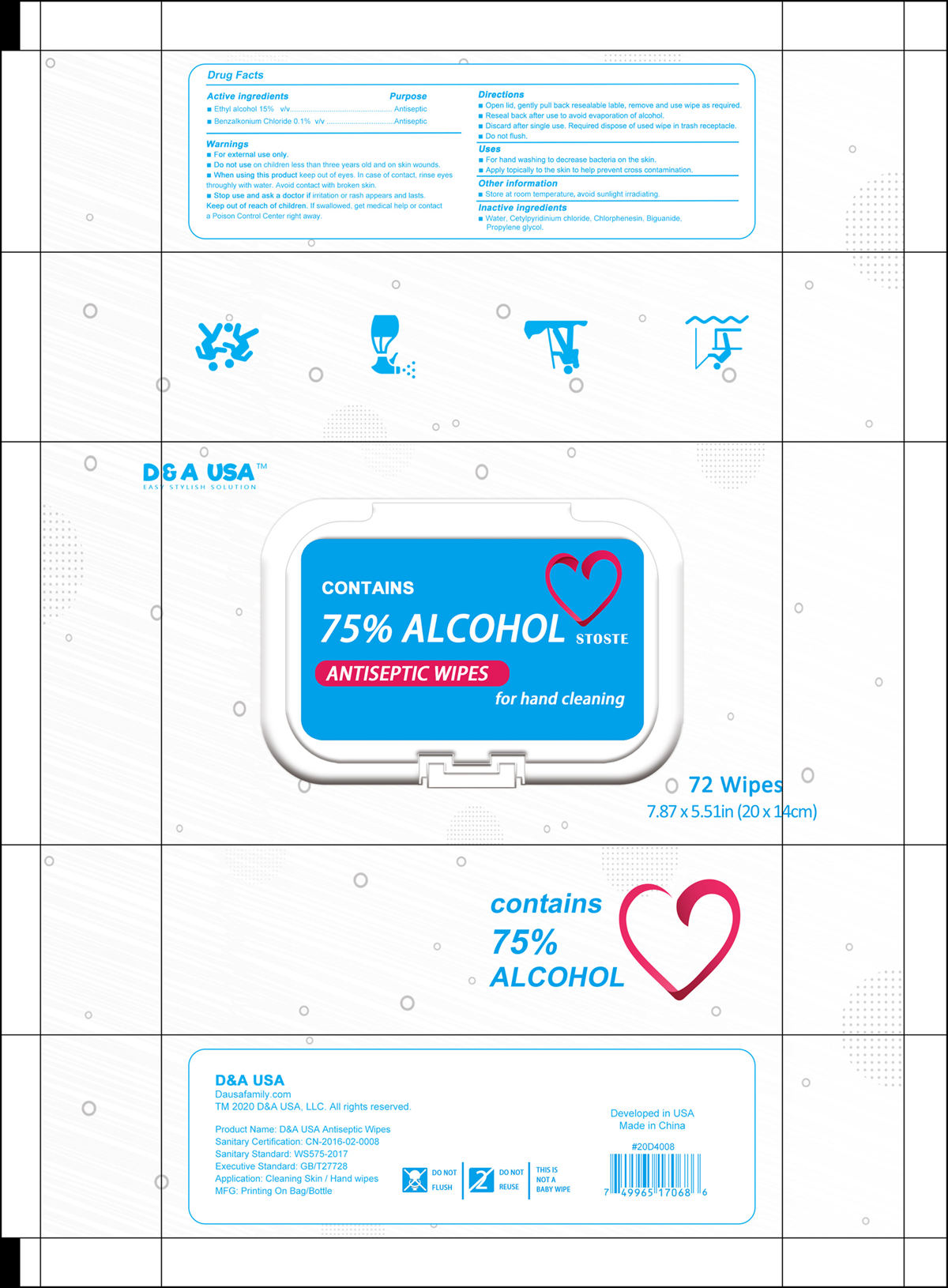 DRUG LABEL: ANTISEPTIC WIPES
NDC: 80168-001 | Form: CLOTH
Manufacturer: D&A USA, LLC
Category: otc | Type: HUMAN OTC DRUG LABEL
Date: 20200913

ACTIVE INGREDIENTS: BENZALKONIUM CHLORIDE 0.1 g/100 mL; ALCOHOL 15 mL/100 mL
INACTIVE INGREDIENTS: PROPYLENE GLYCOL; BIGUANIDE; CETYLPYRIDINIUM CHLORIDE; CHLORPHENESIN; WATER

ACTIVE INGREDIENTS

Ethyl alcohol 15%. Purpose: Antiseptic

Benzalkonium Chloride 0.1%. Purpose: Antiseptic

PURPOSE

Antiseptic

WARNINGS

- For external use only.

DO NOT USE

on children less than three years old and on skin wounds.

WHEN USING THIS PRODUCT

Keep out of eyes. In case of contact, rinse eyes thoroughly with water. Avoid contact with broken skin.

STOP USE AND ASK A DOCTOR IF

irritation or rash appears and lasts.

KEEP OUT OF REACH OF CHILDREN

If swallowed, get medical help or contact a Poison Control Center right away.

DIRECTIONS

- Open lid, gently pull back resealable label, remove and use wipe as required.
- Reseal back after use to avoid evaporation of alcohol.
- Discard after single use. Required dispose of used wipe in trash receptable.
- Do not flush.

USES

- For hand washing to decrease bacteria on the skin.
- Apply topically to the skin to help prevent cross contamination.

OTHER INFORMATION

Store at room temperature, avoid sunlight irradiating.

INACTIVE INGREDIENTS

Water, Cetylpyridinium chloride, Chlorphenesin, Biguanide, Propylene glycol

PACKAGE LABEL - PRINCIPAL DISPLAY PANEL

72 PCS NDC: 80168-001-01

D&A USA

CONTAINS

75% ALCOHOL STOSTE

ANTISEPTIC WIPES

for hand cleaning

72 Wipes

7.87 x 5.51 in (20 x 14 cm)